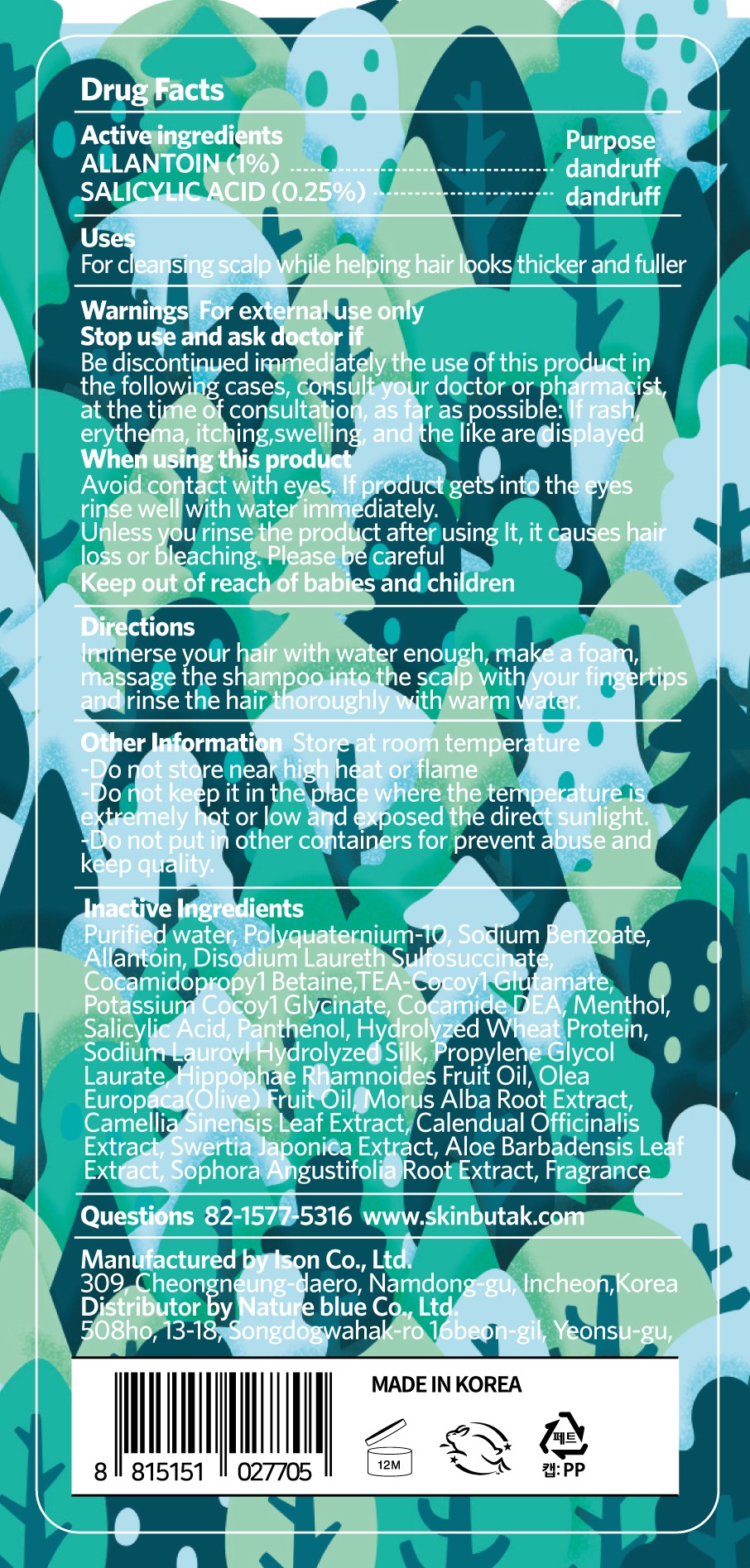 DRUG LABEL: SKINBUTAK CHOMCHOM MAGICSHAMPOO
NDC: 81851-205 | Form: SHAMPOO
Manufacturer: NatureBlue Co.,Ltd
Category: otc | Type: HUMAN OTC DRUG LABEL
Date: 20210429

ACTIVE INGREDIENTS: SALICYLIC ACID 0.25 mg/100 mL; ALLANTOIN 1 mg/100 mL
INACTIVE INGREDIENTS: DISODIUM LAURETH SULFOSUCCINATE; MENTHOL, UNSPECIFIED FORM; HYDROLYZED WHEAT PROTEIN (ENZYMATIC, 3000 MW); GREEN TEA LEAF; POTASSIUM COCOYL GLYCINATE; PROPYLENE GLYCOL MONOLAURATE; HIPPOPHAE RHAMNOIDES FRUIT OIL; OLIVE OIL; CALENDULA OFFICINALIS FLOWER; TRIETHANOLAMINE COCOYL GLUTAMATE; PANTHENOL; MORUS ALBA ROOT; SWERTIA JAPONICA WHOLE FLOWERING; ALOE VERA LEAF; WATER; SODIUM BENZOATE; COCAMIDOPROPYL BETAINE; SOPHORA FLAVESCENS ROOT; COCO DIETHANOLAMIDE

81851-205 SKINBUTAK CHOMCHOM MAGIC SHAMPOO

Active ingredients

ALLANTOIN (1%)
SALICYLIC ACID (0.25%)

Purpose

dandruff

Uses

For cleansing scalp while helping hair looks thicker and fuller

Warnings

For external use only

Stop use and ask doctor if

Be discontinued immediately the use of this product in the following cases, consult your doctor or pharmacist, at the time of consultation, as far as possible: If rash, erythema, itching,swelling, and the like are displayed

When using this product

Avoid contact with eyes. If product gets into the eyes rinse well with water immediately.
Unless you rinse the product after using It, it causes hair loss or bleaching. Please be careful

Keep out of reach of children

Keep out of reach of babies and children

Directions

Immerse your hair with water enough, make a foam, massage the shampoo into the scalp with your fingertips and rinse the hair thoroughly with warm water.

Inactive Ingredients

Purified water, Polyquaternium-10, Sodium Benzoate, Allantoin, Disodium Laureth Sulfosuccinate, Cocamidopropy1 Betaine,TEA-Cocoy1 Glutamate, Potassium Cocoy1 Glycinate, Cocamide DEA, Menthol, Salicylic Acid, Panthenol, Hydrolyzed Wheat Protein, Sodium Lauroyl Hydrolyzed Silk, Propylene Glycol Laurate, Hippophae Rhamnoides Fruit Oil, Olea Europaca(Olive) Fruit Oil, Morus Alba Root Extract, Camellia Sinensis Leaf Extract, Calendual Officinalis Extract, Swertia Japonica Extract, Aloe Barbadensis Leaf Extract, Sophora Angustifolia Root Extract, Fragrance

Other Information

Store at room temperature
-Do not store near high heat or flame
-Do not keep it in the place where the temperature is extremely hot or low and exposed the direct sunlight.
-Do not put in other containers for prevent abuse and keep quality.